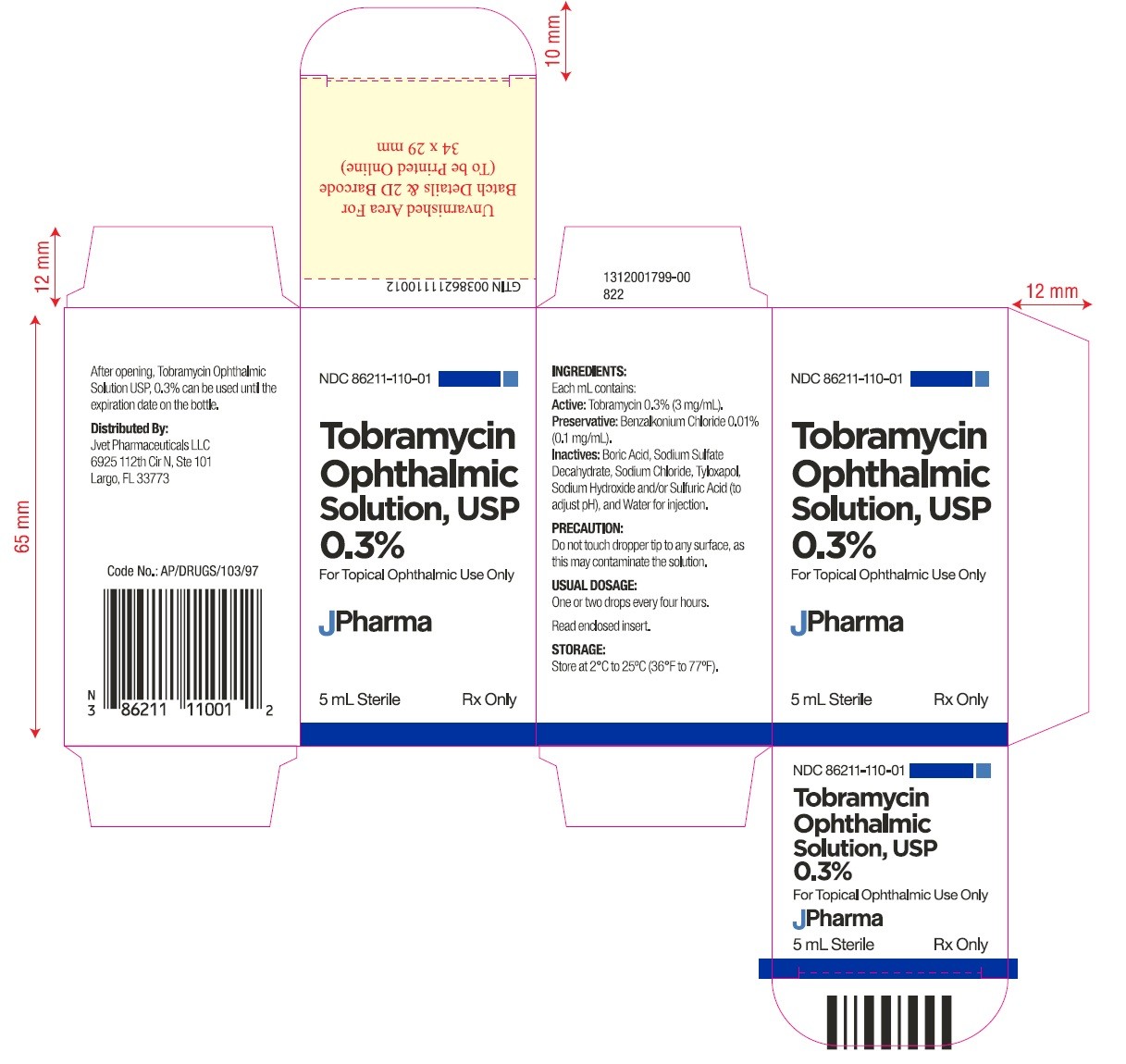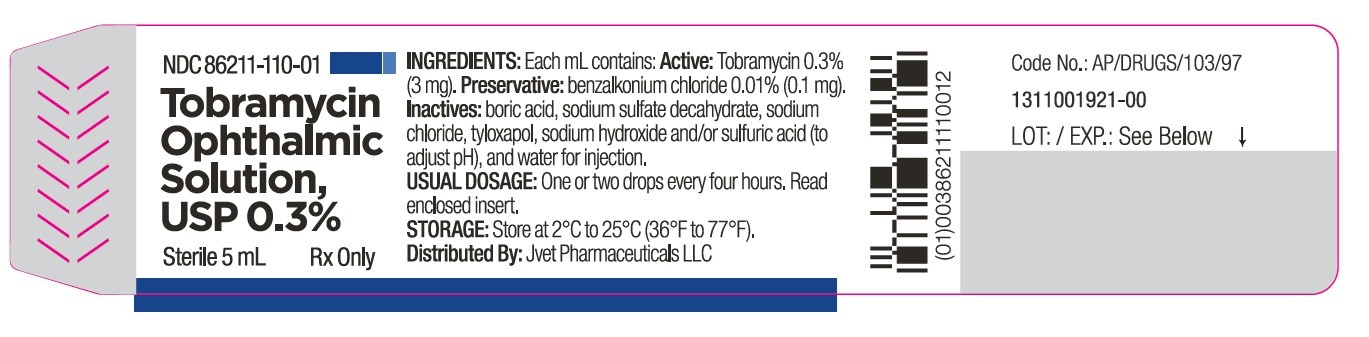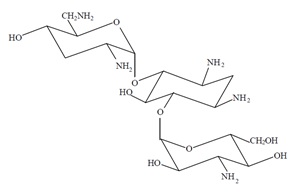 DRUG LABEL: Tobramycin
NDC: 86211-110 | Form: SOLUTION/ DROPS
Manufacturer: JVET PHARMACEUTICALS LLC
Category: prescription | Type: HUMAN PRESCRIPTION DRUG LABEL
Date: 20260126

ACTIVE INGREDIENTS: TOBRAMYCIN 3 mg/1 mL
INACTIVE INGREDIENTS: BENZALKONIUM CHLORIDE; BORIC ACID; SODIUM SULFATE; SODIUM CHLORIDE; TYLOXAPOL; SODIUM HYDROXIDE; SULFURIC ACID; WATER

TOBRAMYCIN OPHTHALMIC SOLUTION USP, 0.3 %

DESCRIPTION

Tobramycin ophthalmic solution USP, 0.3% is a sterile topical ophthalmic antibiotic formulation prepared specifically for topical therapy of external ophthalmic infections.
Each mL of tobramycin ophthalmic solution USP, 0.3% contains: Active: tobramycin 0.3 % (3 mg). Preservative: benzalkonium chloride 0.01 % (0.1 mg). Inactives: boric acid, sodium sulfate decahydrate, sodium chloride, tyloxapol, sodium hydroxide and/or sulfuric acid (to adjust pH) and water for injection. Tobramycin ophthalmic solution USP, 0.3% has a pH range between 7.0 and 8.0 and an osmolality of 260-320 mOsm/kg.
Tobramycin is a water-soluble aminoglycoside antibiotic active against a wide variety of gram-negative and gram-positive ophthalmic pathogens.

The chemical structure of tobramycin is:

Molecular Weight = 467.52
Molecular Formula: C18H37N5O9
Chemical name:
O-3-Amino-3-deoxy-α-D-glucopyranosyl-(1→4)-O-[2,6-diamino-2,3,6-trideoxy-α-D-ribo-hexopyranosyl-(1→6)]-2-deoxy-L-streptamine.

CLINICAL PHARMACOLOGY

In Vitro Data: In vitro studies have demonstrated tobramycin is active against susceptible strains of the following microorganisms: Staphylococci, including S. aureus and S. epidermidis (coagulase-positive and coagulase-negative), including penicillin-resistant strains.

Streptococci, including some of the Group A-beta-hemolytic species, some nonhemolytic species, and some Streptococcus pneumoniae.

Pseudomonas aeruginosa, Escherichia coli, Klebsiella pneumoniae, Enterobacter aerogenes, Proteus mirabilis, Morganella morganii, most Proteus vulgaris strains, Haemophilus influenzae and H. aegyptius, Moraxella lacunata, Acinetobacter calcoaceticus and some Neisseria species. Bacterial susceptibility studies demonstrate that in some cases, microorganisms resistant to gentamicin retain susceptibility to tobramycin.

INDICATIONS AND USAGE

Tobramycin ophthalmic solution 0.3% is a topical antibiotic indicated in the treatment of external infections of the eye and its adnexa caused by susceptible bacteria. Appropriate monitoring of bacterial response to topical antibiotic therapy should accompany the use of tobramycin ophthalmic solution 0.3%. Clinical studies have shown tobramycin to be safe and effective for use in children.

CONTRAINDICATIONS

Tobramycin ophthalmic solution 0.3% is contraindicated in patients with known hypersensitivity to any of its components.

WARNINGS

FOR TOPICAL OPHTHALMIC USE. NOT FOR INJECTION INTO THE EYE. Sensitivity to topically applied aminoglycosides may occur in some patients. Severity of hypersensitivity reactions may vary from local effects to generalized reactions such as erythema, itching, urticaria, skin rash, anaphylaxis, anaphylactoid reactions, or bullous reactions. If a sensitivity reaction to tobramycin ophthalmic solution 0.3% occurs, discontinue use.

PRECAUTIONS

General: As with other antibiotic preparations, prolonged use may result in overgrowth of nonsusceptible organisms, including fungi. If superinfection occurs, appropriate therapy should be initiated.

Cross-sensitivity to other aminoglycoside antibiotics may occur; if hypersensitivity develops with this product, discontinue use and institute appropriate therapy. Patients should be advised not to wear contact lenses if they have signs and symptoms of bacterial ocular infection.

Information for Patients: Do not touch dropper tip to any surface, as this may contaminate the solution.

Pregnancy: Reproduction studies in 3 types of animals at doses up to 33 times the normal human systemic dose have revealed no evidence of impaired fertility or harm to the fetus due to tobramycin. There are, however, no adequate and well-controlled studies in pregnant women. Because animal studies are not always predictive of human response, this drug should be used during pregnancy only if clearly needed.
Nursing Mothers: Because of the potential for adverse reactions in nursing infants from tobramycin ophthalmic solution, a decision should be made whether to discontinue nursing the infant or discontinue the drug, taking into account the importance of the drug to the mother.

Pediatric Use: Safety and effectiveness in pediatric patients below the age of 2 months has not been established.

Geriatric Use: No overall differences in safety or effectiveness have been observed between elderly and younger patients.

ADVERSE REACTIONS

The most frequent adverse reactions to tobramycin ophthalmic solution 0.3% are hypersensitivity and localized ocular toxicity, including lid itching and swelling, and conjunctival erythema. These reactions occur in less than three of 100 patients treated with tobramycin ophthalmic solution.

Postmarketing Experience: Additional adverse reactions identified from post-marketing use include anaphylactic reaction, Stevens-Johnson syndrome, and erythema multiforme.

The following additional adverse reactions have been reported with systemic aminoglycosides: Neurotoxicity, ototoxicity and nephrotoxicity have occurred in patients receiving systemic aminoglycoside therapy. Aminoglycosides may aggravate muscle weakness in patients with known or suspected neuromuscular disorders, such as myasthenia gravis or Parkinson’s disease, because of their potential effect on neuromuscular function.

To report SUSPECTED ADVERSE REACTIONS, contact Jvet Pharmaceuticals, LLC at 1-727-292-1166 or FDA at 1-800-FDA-1088 or www.fda.gov/medwatch.

DOSAGE AND ADMINISTRATION

In mild to moderate disease, instill 1 or 2 drops into the affected eye(s) every 4 hours. In severe infections, instill 2 drops into the eye(s) hourly until improvement, following which treatment should be reduced prior to discontinuation.

HOW SUPPLIED

5 mL sterile solution supplied in opaque white low density polyethylene bottle which is closed with natural low density polyethylene nozzle and then with Tan colored high density polyethylene cap as follows:

5 mL containing tobramycin 0.3% (3 mg/mL)……….. NDC 86211-110-01
Storage: Store at 2°C to 25°C (36°F to 77°F).

After opening, Tobramycin Ophthalmic Solution, USP 0.3% can be used until the expiration date on the bottle.

Distributed by:
Jvet Pharmaceuticals LLC

6925112th Circle North, Suite 101

Largo, FL 33773

Revised: May 2025

L110I-VTN R-2505

747

1313001232-00

PACKAGE LABEL.PRINCIPAL DISPLAY PANEL

Bottle Label:
NDC 86211-110-01
Tobramycin Ophthalmic solution, USP 0.3%
Sterile 5 mL Rx Only

Carton Label:

NDC 86211-110-01
Tobramycin Ophthalmic solution, USP 0.3%
5 mL Sterile Rx Only